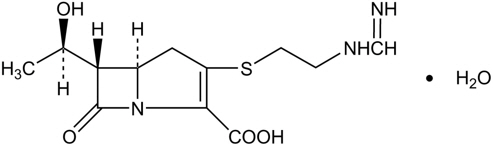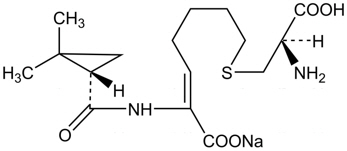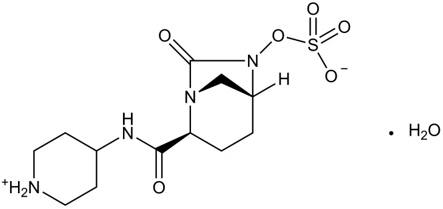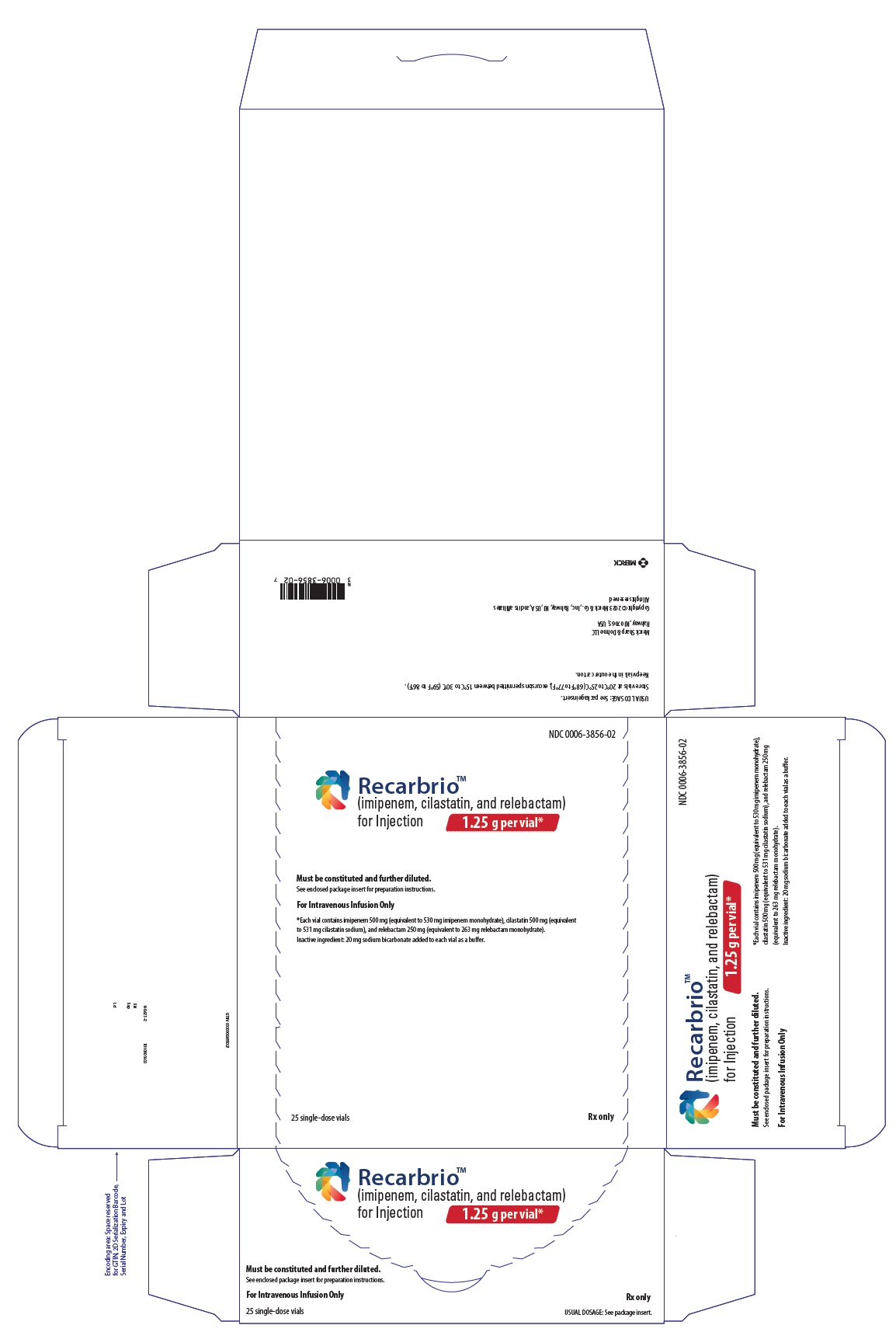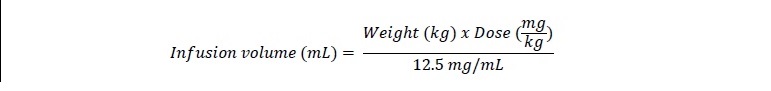 DRUG LABEL: RECARBRIO
NDC: 0006-3856 | Form: INJECTION, POWDER, FOR SOLUTION
Manufacturer: Merck Sharp & Dohme LLC
Category: prescription | Type: HUMAN PRESCRIPTION DRUG LABEL
Date: 20251209

ACTIVE INGREDIENTS: IMIPENEM ANHYDROUS 500 mg/100 mL; CILASTATIN 500 mg/100 mL; RELEBACTAM ANHYDROUS 250 mg/100 mL
INACTIVE INGREDIENTS: SODIUM BICARBONATE 20 mg/100 mL

HIGHLIGHTS OF PRESCRIBING INFORMATION

These highlights do not include all the information needed to use RECARBRIO safely and effectively. See full prescribing information for RECARBRIO.
RECARBRIO® (imipenem, cilastatin, and relebactam) for injection, for intravenous use
Initial U.S. Approval: 2019

RECENT MAJOR CHANGES

Indications and Usage (1) | 12/2025
Dosage and Administration (2) | 12/2025

1 INDICATIONS AND USAGE

RECARBRIO is a combination of imipenem, a penem antibacterial, cilastatin, a renal dehydropeptidase inhibitor, and relebactam, a beta-lactamase inhibitor, indicated in adult and pediatric patients weighing at least 2 kg for the treatment of the following infections caused by susceptible gram-negative microorganisms:

- Hospital-acquired bacterial pneumonia and ventilator-associated bacterial pneumonia (HABP/VABP). (1.1)
- Complicated urinary tract infections, including pyelonephritis (cUTI) in patients who have limited or no alternative treatment options. (1.2)
- Complicated intra-abdominal infections (cIAI) in patients who have limited or no alternative treatment options. (1.3)

Approval of the cUTI and cIAI indications is based on limited clinical safety and efficacy data for RECARBRIO. (1.2, 1.3, 14)

Limitations of Use

- RECARBRIO is not recommended in pediatric patients less than 37 weeks post-menstrual age (gestational age at birth plus post-natal age). (1.4, 2.2).
- RECARBRIO is not recommended in pediatric patients weighing less than 30 kg with renal impairment. (1.4, 2.3).

Usage to Reduce Development of Drug-Resistant Bacteria

To reduce the development of drug-resistant bacteria and maintain the effectiveness of RECARBRIO and other antibacterial drugs, RECARBRIO should be used only to treat or prevent infections that are proven or strongly suspected to be caused by bacteria. (1.5)

2 DOSAGE AND ADMINISTRATION

- Adult Patients: The recommended dosage of RECARBRIO is 1.25 grams (imipenem 500 mg, cilastatin 500 mg, relebactam 250 mg) administered by intravenous (IV) infusion over 30 minutes every 6 hours to adult patients with creatinine clearance (CLcr) 90 mL/min or greater. (2.1)
- Pediatric Patients weighing at least 2 kg: The recommended dosage of RECARBRIO for pediatric patients weighing at least 2kg varies by patient weight and age, with specific dosing recommendations as shown in the table below, (2.2):

Recommended Dosage of RECARBRIO In Pediatric Patients Weighing at Least 2 kg
Age Range | Body Weight | Dose | Dosing Frequency | Infusion Duration
Birth [Pediatric patients from birth (includes pediatric patients at least 37 weeks post-menstrual age)] to less than 3 months | 2 kg or greater | RECARBRIO 37.5 [Provides 15 mg/kg imipenem, 15 mg/kg cilastatin, and 7.5 mg/kg relebactam] mg/kg | Every 8 hours | 60 minutes
3 months to less than 18 years | less than 30 kg | RECARBRIO 37.5 mg/kg | Every 6 hours | 60 minutes
3 months to less than 18 years | 30 kg or greater | RECARBRIO 1.25 [Provides 500 mg imipenem, 500 mg cilastatin, and 250 mg, relebactam] grams | Every 6 hours | 30 minutes

- Dose reduction is required in adult and pediatric (weighing at least 30 kg) patients with renal impairment. (2.3, 2.4)
- Do not administer RECARBRIO to adults with CLcr less than 15 mL/min unless hemodialysis is instituted within 48 hours after dose administration. (2.3)
- Do not administer RECARBRIO to pediatric patients weighing at least 30 kg with an eGFR less than 15 mL/min/1.73m^2 unless hemodialysis is instituted within 48 hours after dose administration. (2.4)
- See Full Prescribing Information for instructions for constituting supplied dry powder and subsequent required dilution. (2.5)
- See Full Prescribing Information for drug compatibilities and incompatibilities. (2.7, 2.8)

3 DOSAGE FORMS AND STRENGTHS

RECARBRIO 1.25 grams for injection is supplied as sterile powder for constitution in a single-dose vial containing imipenem 500 mg (anhydrate equivalent), cilastatin 500 mg (free acid equivalent), and relebactam 250 mg (anhydrate equivalent). (3)

4 CONTRAINDICATIONS

RECARBRIO is contraindicated in patients with a history of known severe hypersensitivity to any component of RECARBRIO. (4)

5 WARNINGS AND PRECAUTIONS

- Hypersensitivity Reactions: Serious and occasionally fatal hypersensitivity (anaphylactic) reactions have been reported in patients receiving beta lactam drugs. Discontinue RECARBRIO immediately if a hypersensitivity reaction occurs. (5.1)
- Seizures and Central Nervous System Adverse Reactions: CNS adverse reactions such as seizures have been reported with imipenem/cilastatin, a component of RECARBRIO. If focal tremors, myoclonus, or seizures occur, evaluate patients, to determine whether RECARBRIO should be discontinued. (5.2)
- Increased Seizure Potential Due to Interaction with Valproic Acid: Concomitant use of RECARBRIO with valproic acid or divalproex sodium may reduce the serum concentration of valproic acid which may increase the risk of breakthrough seizures. Avoid concomitant use or consider alternative antibacterial drugs other than carbapenems. (5.3, 7.2)
- Clostridioides difficile-Associated Diarrhea (CDAD): Has been reported with RECARBRIO. Evaluate if diarrhea occurs. (5.4)

6 ADVERSE REACTIONS

- Adult HABP/VABP Patients: The most frequently reported adverse reactions occurring in greater than or equal to 5% of patients treated with RECARBRIO were aspartate aminotransferase increased, anemia, alanine aminotransferase increased, diarrhea, hypokalemia, and hyponatremia. (6)
- Adult cUTI and cIAI Patients: The most frequently reported adverse reactions occurring in greater than or equal to 2% of patients treated with imipenem/cilastatin plus relebactam 250 mg, the components of RECARBRIO, were diarrhea, nausea, headache, vomiting, alanine aminotransferase increased, aspartate aminotransferase increased, phlebitis/infusion site reactions, pyrexia, and hypertension. (6)
- Pediatric HABP/VABP, cUTI, and cIAI Patients: The most frequently reported adverse reactions occurring in greater than 3% of pediatric patients treated with RECARBRIO were vomiting, diarrhea, nausea, headache, phlebitis/infusion site reactions, and rash.

To report SUSPECTED ADVERSE REACTIONS, contact Merck Sharp & Dohme LLC at 1-877-888-4231 or FDA at 1-800-FDA-1088 or www.fda.gov/medwatch.

7 DRUG INTERACTIONS

- Ganciclovir: Avoid concomitant use. (7.1)
- Valproic Acid or Divalproex Sodium: Avoid concomitant use. (7.2)

FULL PRESCRIBING INFORMATION

1 INDICATIONS AND USAGE

1.1 Hospital-acquired Bacterial Pneumonia and Ventilator-associated Bacterial Pneumonia (HABP/VABP)

RECARBRIO® is indicated in adult and pediatric patients weighing at least 2 kg for the treatment of hospital-acquired bacterial pneumonia and ventilator-associated bacterial pneumonia, caused by the following susceptible gram-negative microorganisms: Acinetobacter calcoaceticus-baumannii complex, Enterobacter cloacae, Escherichia coli, Haemophilus influenzae, Klebsiella aerogenes, Klebsiella oxytoca, Klebsiella pneumoniae, Pseudomonas aeruginosa, and Serratia marcescens.

1.2 Complicated Urinary Tract Infections (cUTI), including Pyelonephritis

RECARBRIO is indicated in adult and pediatric patients weighing at least 2 kg who have limited or no alternative treatment options, for the treatment of complicated urinary tract infections (cUTI), including pyelonephritis, caused by the following susceptible gram-negative microorganisms: Enterobacter cloacae, Escherichia coli, Klebsiella aerogenes, Klebsiella pneumoniae, and Pseudomonas aeruginosa.

Approval of this indication is based on limited clinical safety and efficacy data for RECARBRIO [see Clinical Studies (14.2)].

1.3 Complicated Intra-abdominal Infections (cIAI)

RECARBRIO is indicated in adult and pediatric patients weighing at least 2 kg who have limited or no alternative treatment options for the treatment of complicated intra-abdominal infections (cIAI) caused by the following susceptible gram-negative microorganisms: Bacteroides caccae, Bacteroides fragilis, Bacteroides ovatus, Bacteroides stercoris, Bacteroides thetaiotaomicron, Bacteroides uniformis, Bacteroides vulgatus, Citrobacter freundii, Enterobacter cloacae, Escherichia coli, Fusobacterium nucleatum, Klebsiella aerogenes, Klebsiella oxytoca, Klebsiella pneumoniae, Parabacteroides distasonis, and Pseudomonas aeruginosa.

Approval of this indication is based on limited clinical safety and efficacy data for RECARBRIO [see Clinical Studies (14.2)].

1.4 Limitations of Use

- RECARBRIO is not recommended in pediatric patients less than 37 weeks post-menstrual age (gestational age at birth plus post-natal age) [see Dosage and Administration (2.2) and Use in Specific Populations (8.4)].
- RECARBRIO is not recommended in pediatric patients weighing less than 30 kg with renal impairment [see Dosage and Administration (2.4), Use in Specific Populations (8.4, 8.6) and Clinical Pharmacology (12.3)].

1.5 Usage to Reduce Development of Drug-Resistant Bacteria

To reduce the development of drug-resistant bacteria and maintain the effectiveness of RECARBRIO and other antibacterial drugs, RECARBRIO should be used only to treat or prevent infections that are proven or strongly suspected to be caused by susceptible bacteria. When culture and susceptibility information are available, they should be considered in selecting or modifying antibacterial therapy. In the absence of such data, local epidemiology and susceptibility patterns may contribute to the empiric selection of therapy.

2 DOSAGE AND ADMINISTRATION

2.1 Recommended Dosage in Adult Patients

The recommended dosage of RECARBRIO is 1.25 grams (imipenem 500 mg, cilastatin 500 mg, and relebactam 250 mg) administered by intravenous (IV) infusion over 30 minutes every 6 hours in adult patients with creatinine clearance (CLcr) of 90 mL/min or greater). The recommended duration of treatment with RECARBRIO is 4 days to 14 days. The duration of therapy should be guided by the severity and location of infection and clinical response.

2.2 Recommended Dosage in Pediatric Patients Weighing at Least 2 kg

The recommended dosage of RECARBRIO in pediatric patients weighing at least 2 kg varies by patient weight and age, with specific dosing recommendations shown in Table 1. The recommended duration of treatment with RECARBRIO is 4 days to 14 days. The duration of therapy should be guided by the severity and location of infection and clinical response.

RECARBRIO is not recommended in pediatric patients less than 37 weeks post-menstrual age (gestational age at birth plus post-natal age) [see Indications and Usage (1.4) and Use in Specific Populations (8.4)].

RECARBRIO is not recommended for pediatric patients weighing less than 30 kg with renal impairment [see Dosage and administration (2.4) and Use in Specific Populations (8.4)].

Table 1: Recommended Dosage of RECARBRIO In Pediatric Patients Weighing at Least 2 kg
Age Range | Body Weight | Dose | Dosing Frequency | Infusion Duration
Birth [Pediatric patients from birth (includes pediatric patients at least 37 weeks post-menstrual age)] to less than 3 months | 2 kg or greater | RECARBRIO 37.5 [Provides 15 mg/kg imipenem, 15 mg/kg cilastatin, and 7.5 mg/kg relebactam] mg/kg | Every 8 hours | 60 minutes
3 months to less than 18 years | less than 30 kg | RECARBRIO 37.5 mg/kg | Every 6 hours | 60 minutes
3 months to less than 18 years | 30 kg or greater | RECARBRIO 1.25 [Provides 500 mg imipenem, 500 mg cilastatin, and 250 mg, relebactam] grams | Every 6 hours | 30 minutes

2.3 Recommended Dosage in Adult Patients with Renal Impairment

Adult patients who have a CLcr less than 90 mL/min require dosage reduction of RECARBRIO. The recommended dosage of RECARBRIO in adult patients with renal impairment is shown in Table 2.

Table 2: Recommended Dosage of RECARBRIO in Adult Patients with Renal Impairment
Creatinine Clearance (CLcr) ([mL/min)] [CLcr calculated using the Cockcroft-Gault formula for adult patients.] | Dose [RECARBRIO is provided as a single vial in a fixed-dose combination; the dose for each component will be adjusted equally during preparation [see Dosage and Administration (2.5)].] | Dosing Frequency | Infusion Duration
60 to 89 | RECARBRIO 1 gram [Provides 400 mg imipenem, 400 mg cilastatin, and 200 mg relebactam] | Every 6 hours | 30 minutes
30 to 59 | RECARBRIO 0.75 grams [Provides 300 mg imipenem, 300 mg cilastatin, and 150 mg relebactam] | Every 6 hours | 30 minutes
15 to 29 not receiving hemodialysis | RECARBRIO 0.5 grams [Provides 200 mg imipenem, 200 mg cilastatin, and 100 mg relebactam] | Every 6 hours | 30 minutes
Receiving hemodialysis [Administration should be timed to follow hemodialysis and at intervals timed from the end of that hemodialysis session.] | RECARBRIO 0.5 grams | Every 6 hours | 30 minutes
Less than 15 not receiving hemodialysis | Not recommended

Do not administer RECARBRIO to adult patients with CLcr less than 15 mL/min unless hemodialysis is instituted within 48 hours after dose administration.

Imipenem, cilastatin, and relebactam are cleared from the circulation during hemodialysis. For adult patients maintained on hemodialysis, administer the recommended dose of RECARBRIO after hemodialysis and at intervals timed from the end of that hemodialysis session.

There is inadequate information to recommend dosage of RECARBRIO for adults undergoing peritoneal dialysis.

2.4 Recommended Dosage in Pediatric Patients Weighing at Least 30 kg with Renal Impairment

Pediatric patients weighing at least 30 kg who have an estimated glomerular filtration rate (eGFR) less than 90 mL/min/1.73m^2 require dosage reduction of RECARBRIO. The recommended dosage of RECARBRIO in pediatric patients weighing at least 30 kg with renal impairment is shown in Table 3. There is insufficient information to recommend a dosage of RECARBRIO for pediatric patients weighing less than 30 kg with any degree of renal impairment.

Table 3. Recommended Dosage of RECARBRIO in Pediatric Patients Weighing at Least 30 kg with Renal Impairment
eGFR (mL/min/1.73 m^2) [Calculated using a GFR estimating equation validated in pediatric patients weighing at least 30 kg.] | Recommended Dose [RECARBRIO is provided as a single vial in a fixed-dose combination; the dose for each component will be adjusted equally during preparation [see Dosage and Administration (2.5)].] | Dosing Frequency | Infusion Duration
60 to 89 | RECARBRIO 1 gram [Provides 400 mg imipenem, 400 mg cilastatin, and 200 mg relebactam] | Every 6 hours | 30 minutes
30 to 59 | RECARBRIO 0.75 grams [Provides 300 mg imipenem, 300 mg cilastatin, and 150 mg relebactam] | Every 6 hours | 30 minutes
15 to 29 not receiving hemodialysis | RECARBRIO 0.5 grams [Provides 200 mg imipenem, 200 mg cilastatin, and 100 mg relebactam] | Every 6 hours | 30 minutes
Receiving hemodialysis [Administration should be timed to follow hemodialysis and at intervals timed from the end of that hemodialysis session.] | RECARBRIO 0.5 grams | Every 6 hours | 30 minutes
Less than 15 not receiving hemodialysis | Not recommended

Do not administer RECARBRIO to pediatric patients weighing at least 30 kg with an eGFR less than 15 mL/min/1.73m^2 unless hemodialysis is instituted within 48 hours after dose administration.

Imipenem, cilastatin, and relebactam are cleared from the circulation during hemodialysis. For pediatric patients weighing at least 30 kg maintained on hemodialysis, administer the recommended dose of RECARBRIO after hemodialysis and at intervals timed from the end of that hemodialysis session.

There is inadequate information to recommend a dosage of RECARBRIO for pediatric patients undergoing peritoneal dialysis.

2.5 Preparation of RECARBRIO Solution for Intravenous Administration

RECARBRIO is supplied as a dry powder in a single-dose vial that must be constituted and further diluted using aseptic technique prior to intravenous infusion. To prepare the infusion solution, contents of the vial must be constituted with the appropriate diluent as instructed below. A list of appropriate diluents is as follows:

- 0.9% Sodium Chloride Injection, USP
- 5% Dextrose Injection, USP
- 5% Dextrose Injection, USP + 0.9% Sodium Chloride Injection, USP
- 5% Dextrose Injection, USP + 0.45% Sodium Chloride Injection, USP
- 5% Dextrose Injection, USP + 0.225% Sodium Chloride Injection, USP

RECARBRIO has low aqueous solubility. To ensure complete dissolution of RECARBRIO it is important to adhere to the following instructions:

Step 1) For diluents available in 100 mL prefilled infusion bags, proceed to step 2. For diluents not available in 100 mL prefilled infusion bags, aseptically withdraw 100 mL of the desired diluent and transfer it to an empty infusion bag, then proceed to step 2.
Step 2) Withdraw 20 mL (as two 10 mL aliquots) of diluent from the appropriate infusion bag and constitute the vial with one 10 mL aliquot of the diluent. The constituted suspension is for intravenous infusion only after dilution in an appropriate infusion solution.
Step 3) After constitution, shake vial well and transfer resulting suspension into the remaining 80 mL of the infusion bag.
Step 4) Add the second 10 mL aliquot of infusion diluent to the vial and shake well to ensure complete transfer of vial contents; repeat transfer of the resulting suspension to the infusion solution before administering. Agitate the resulting mixture until clear.

Constituted solutions of RECARBRIO range from colorless to yellow. Variations of color within this range do not affect the potency of the product.

Parenteral drug products should be inspected visually for particulate matter and discoloration prior to administration, whenever solution and container permit. Discard if discoloration or visible particles are observed.

The above instructions for preparation of RECARBRIO solution for intravenous administration must be followed for all patients, irrespective of the intended patient’s renal function, age or weight.

The volume of this prepared RECARBRIO solution to be administered in adult and pediatric (weighing at least 30 kg) patients is determined based on estimated renal function [see Dosage and Administration (2.6)].

The volume of the prepared RECARBRIO solution to be administered to pediatric patients weighing 2 kg to less than 30 kg with normal renal function is calculated based on patient weight using the formula below [see Dosage and Administration (2.2)]:

To achieve the appropriate infusion volume, withdraw and discard the excess (100 mL minus the infusion volume) from the prepared 100 mL solution. The remaining volume is the appropriate infusion volume.

2.6 Preparation of RECARBRIO Solution for Intravenous Administration in Adult and Pediatric Patients Weighing at Least 30 kg with Renal Impairment

Prepare a reduced dose of RECARBRIO (1 gram, 0.75 grams, or 0.5 grams) [see Dosage and Administration (2.3, 2.4)] by preparing a 100 mL solution containing 1.25 grams as described above [see Dosage and Administration (2.5)] then withdrawing and discarding the excess according to Table 4.

Table 4: Preparation of Reduced RECARBRIO Doses for Intravenous Administration in Adult and Pediatric Patients Weighing at Least 30 kg with Renal Impairment
Estimated Renal Function Creatinine Clearance (mL/min) [Calculated using the Cockcroft-Gault formula for adult patients] Or Estimated Glomerular Filtration Rate eGFR (mL/min/1.73 m^2) [Calculated using a GFR estimating equation validated in pediatric patients weighing at least 30 kg] | Dose | After preparation as instructed above, remove from the 100 mL prepared bag the volume indicated below and discard | Resulting volume that provides the indicated reduced dose
60 to 89 | RECARBRIO 1 gram [Provides 400 mg imipenem, 400 mg cilastatin, and 200 mg relebactam] | 20 mL | 80 mL
30 to 59 | RECARBRIO 0.75 grams [Provides 300 mg imipenem, 300 mg cilastatin, and 150 mg relebactam] | 40 mL | 60 mL
15 to 29 not receiving hemodialysis | RECARBRIO 0.5 grams [Provides 200 mg imipenem, 200 mg cilastatin, and 100 mg relebactam] | 60 mL | 40 mL
Receiving hemodialysis | RECARBRIO 0.5 grams | 60 mL | 40 mL

2.7 Storage of Constituted Solution

RECARBRIO, as supplied in single-dose glass vials upon constitution with the appropriate diluent and following further dilution in the infusion bag, maintains satisfactory potency for at least 2 hours at room temperature (up to 30°C) or for at least 24 hours under refrigeration at 2°C to 8°C (36°F to 46°F). Do not freeze solutions of RECARBRIO.

2.8 Compatible Injectable Drug Products

Compatible Drug Products

The physical compatibility of RECARBRIO with selected injectable drug products was evaluated in two commonly available diluents. Compatible drugs with the corresponding compatible diluent (i.e., 5% Dextrose Injection, USP or 0.9% Sodium Chloride Injection, USP) are listed below. RECARBRIO should not be co-administered through the same intravenous line (or cannula), with other drug products not listed below, as no compatibility data are available. Refer to the respective prescribing information of the co-administered drug(s) to confirm compatibility of simultaneous co-administration.

List of Compatible Injectable Drugs for use with 5% Dextrose USP or 0.9% Sodium Chloride USP Injection as Diluents

- dexmedetomidine
- dopamine
- epinephrine
- fentanyl
- heparin
- midazolam
- norepinephrine
- phenylephrine

2.9 Incompatible Injectable Drug Products

RECARBRIO for injection for intravenous infusion is physically incompatible with propofol in 5% Dextrose USP or 0.9% Sodium Chloride USP.

3 DOSAGE FORMS AND STRENGTHS

RECARBRIO (imipenem, cilastatin, and relebactam) for injection, 1.25 grams is supplied as a white to light yellow sterile powder for constitution in a single-dose glass vial containing imipenem 500 mg (equivalent to 530 mg imipenem monohydrate), cilastatin 500 mg (equivalent to 531 mg cilastatin sodium), and relebactam 250 mg (equivalent to 263 mg relebactam monohydrate).

4 CONTRAINDICATIONS

RECARBRIO is contraindicated in patients with a history of known severe hypersensitivity (severe systemic allergic reaction such as anaphylaxis) to any component of RECARBRIO.

5 WARNINGS AND PRECAUTIONS

5.1 Hypersensitivity Reactions

Serious and occasionally fatal hypersensitivity (anaphylactic) reactions have been reported in patients receiving therapy with beta lactams. Before initiating therapy with RECARBRIO, careful inquiry should be made concerning previous hypersensitivity reactions to carbapenems, penicillins, cephalosporins, other beta lactams, and other allergens. If a hypersensitivity reaction to RECARBRIO occurs, discontinue the therapy immediately.

RECARBRIO is contraindicated in patients with a history of severe hypersensitivity to any component of RECARBRIO [see Contraindications (4)].

5.2 Seizures and Other Central Nervous System (CNS) Adverse Reactions

CNS adverse reactions, such as seizures, confusional states, and myoclonic activity, have been reported during treatment with imipenem/cilastatin, a component of RECARBRIO, especially when recommended dosages of imipenem were exceeded. These have been reported most commonly in patients with CNS disorders (e.g., brain lesions or history of seizures) and/or compromised renal function.

Anticonvulsant therapy should be continued in patients with known seizure disorders. If CNS adverse reactions including seizures occur, patients should undergo a neurological evaluation to determine whether RECARBRIO should be discontinued.

5.3 Increased Seizure Potential Due to Interaction with Valproic Acid

Concomitant use of RECARBRIO, with valproic acid or divalproex sodium may increase the risk of breakthrough seizures. Avoid concomitant use of RECARBRIO with valproic acid or divalproex sodium or consider alternative antibacterial drugs other than carbapenems [see Drug Interactions (7.2)].

5.4 Clostridioides difficile-Associated Diarrhea (CDAD)

Clostridioides difficile-associated diarrhea (CDAD) has been reported with use of nearly all antibacterial agents, including RECARBRIO, and may range in severity from mild diarrhea to fatal colitis. Treatment with antibacterial agents alters the normal flora of the colon leading to overgrowth of C. difficile.

C. difficile produces toxins A and B which contribute to the development of CDAD. Hypertoxin producing strains of C. difficile cause increased morbidity and mortality, as these infections can be refractory to antimicrobial therapy and may require colectomy. CDAD must be considered in all patients who present with diarrhea following antibacterial drug use. Careful medical history is necessary since CDAD has been reported to occur over two months after the administration of antibacterial agents.

If CDAD is suspected or confirmed, ongoing antibacterial drug use not directed against C. difficile may need to be discontinued. Appropriate fluid and electrolyte management, protein supplementation, antibacterial drug treatment of C. difficile, and surgical evaluation should be instituted as clinically indicated.

5.5 Development of Drug-resistant Bacteria

Prescribing RECARBRIO in the absence of a proven or strongly suspected bacterial infection or prophylactic indication is unlikely to provide benefit to the patient and increases the risk of the development of drug-resistant bacteria.

6 ADVERSE REACTIONS

The following serious adverse reactions are described in greater detail in the Warnings and Precautions section.

- Hypersensitivity Reactions [see Warnings and Precautions (5.1)]
- Seizures and Other Central Nervous System Adverse Reactions [see Warnings and Precautions (5.2)]
- Increased Seizure Potential Due to Interaction with Valproic Acid [see Warnings and Precautions (5.3)]
- Clostridioides difficile-Associated Diarrhea (CDAD) [see Warnings and Precautions (5.4)]

6.1 Clinical Trials Experience

Because clinical trials are conducted under widely varying conditions, adverse reaction rates observed in the clinical trials of a drug cannot be directly compared to rates in the clinical trials of another drug and may not reflect the rates observed in practice.

Adult Patients

Overview of the Safety Evaluation of RECARBRIO in Adult Patients

Safety was primarily evaluated in three active-controlled, double-blind trials in HABP/VABP, cUTI, and cIAI (Trials 1, 2, and 3, respectively).
In the HABP/VABP trial (Trial 1), patients were treated with either RECARBRIO or piperacillin and tazobactam (4.5 grams).

In the cUTI trial (Trial 2) and cIAI trial (Trial 3), patients in the treatment arms were treated with either imipenem 500 mg/cilastatin 500 mg and relebactam 250 mg or imipenem 500 mg/cilastatin 500 mg and relebactam 125 mg (not an approved dose), and patients in the control arm were treated with imipenem 500 mg/cilastatin 500 mg plus placebo (IV normal saline). Across Trials 2 and 3, the mean duration of IV therapy in patients treated with imipenem/cilastatin plus relebactam 250 mg was approximately 7 days.

Clinical Trial Experience in Adult Patients with HABP/VABP

Trial 1 included 266 adult patients treated with RECARBRIO and 269 patients treated with piperacillin and tazobactam (4.5 grams) administered intravenously over 30 minutes every 6 hours. The mean age was 60 years, 43% of patients were 65 years of age and older, 31% were female and 22% had polymicrobial infection. The mean Acute Physiology and Chronic Health Evaluation (APACHE) II score was 15 and 48% of patients had an APACHE II score greater than or equal to 15 at baseline. Overall, 260 (49%) patients were ventilated at enrollment, including 194 (36%) patients with VABP and 66 (12%) patients with ventilated HABP.

Clinical Trial Experience in Adult Patients with cUTI including, Pyelonephritis

Trial 2 included 198 adult patients treated with imipenem/cilastatin and relebactam (99 patients each with imipenem 500 mg/cilastatin 500 mg plus relebactam 125 mg or relebactam 250 mg) and 100 patients treated with imipenem 500 mg/cilastatin 500 mg, administered intravenously over 30 minutes every 6 hours. After a minimum of 4 days of IV therapy, patients could be switched to oral ciprofloxacin (500 mg daily every 12 hours) to complete the treatment course of 4 to 14 days total (IV plus oral), at the discretion of the investigator. The mean age was 56 years, 40% of patients were 65 years of age and older, 16% were 75 years of age and older, 50% were female, and approximately 18% had moderate to severe renal impairment.

Clinical Trial Experience in Adult Patients with cIAI

Trial 3 included 233 adult patients treated with imipenem/cilastatin plus relebactam (116 subjects with imipenem 500 mg/cilastatin 500 mg and relebactam 125 mg and 117 subjects with imipenem 500 mg/cilastatin 500 mg plus relebactam 250 mg), and 114 patients treated with imipenem 500 mg/cilastatin 500 mg, administered intravenously over 30 minutes every 6 hours for 4 to 14 days, at the discretion of the investigator. The mean age was 49 years, 23% of the patients were 65 years of age and older, 9.8% were 75 years of age and older, and 42% were female.

Serious Adverse Reactions and Adverse Reactions Leading to Discontinuation in Adult Patients

In Trial 1, serious adverse reactions occurred in 27% (71/266) of patients receiving RECARBRIO and 32% (86/269) of patients receiving piperacillin and tazobactam. Adverse reactions leading to death were reported in 15% (40/266) of patients receiving RECARBRIO and 21% (57/269) of patients receiving piperacillin and tazobactam.

Adverse reactions leading to discontinuation occurred in 5.6% (15/266) of patients receiving imipenem 500 mg/cilastatin 500 mg/relebactam 250 mg and 8.2% (22/269) of patients receiving piperacillin and tazobactam.

In Trials 2 and 3, serious adverse reactions occurred in 3.2% (7/216) of patients receiving imipenem 500 mg/cilastatin 500 mg plus relebactam 250 mg and 5.1% (11/214) of patients receiving imipenem 500 mg/cilastatin 500 mg. There were no deaths reported in patients receiving imipenem 500 mg/cilastatin 500 mg plus relebactam 250 mg or imipenem 500 mg/cilastatin 500 mg alone. Deaths were reported in 1.4% (3/215) of patients receiving imipenem 500 mg/cilastatin 500 mg plus relebactam 125 mg (not an approved dose).

Adverse reactions leading to discontinuation occurred in 1.9% (4/216) of patients receiving imipenem 500 mg/cilastatin 500 mg plus relebactam 250 mg and 2.3% (5/214) of patients receiving imipenem 500 mg/cilastatin 500 mg.

Common Adverse Reactions in Adult Patients

In Trial 1, adverse reactions occurred during the protocol-specified follow-up period, which was IV therapy plus 14 days following completion of therapy, in 85% (226/266) of patients receiving RECARBRIO and 87% (233/269) of patients receiving piperacillin and tazobactam. Table 5 lists the most common adverse reactions occurring in ≥4% of patients receiving imipenem 500 mg/cilastatin 500 mg/relebactam 250 mg or piperacillin and tazobactam in Trial 1.

Table 5: Adverse Reactions Occurring in Greater Than or Equal to 4% of HABP/VABP Adult Patients Receiving RECARBRIO in Trial 1
Adverse Reaction | RECARBRIO [RECARBRIO, IV every 6 hours.] (N=266) N (%) | Piperacillin/Tazobactam [Piperacillin 4000 mg and Tazobactam 500 mg (4.5 grams), IV every 6 hours.] (N=269) N (%)
Blood and lymphatic system disorders
Anemia | 28 (10.5%) | 27 (10.0%)
Gastrointestinal disorders
Constipation | 11 (4.1%) | 3 (1.1%)
Diarrhea | 21 (7.9%) | 30 (11.2%)
General disorders and administration site conditions
Pyrexia | 11 (4.1%) | 20 (7.4%)
Laboratory investigations
Alanine aminotransferase increased | 26 (9.8%) | 19 (7.1%)
Aspartate aminotransferase increased | 31 (11.7%) | 20 (7.4%)
Metabolism and nutrition disorders
Hypokalemia [Hypokalemia includes hypokalemia and blood potassium decreased.] | 21 (7.9%) | 26 (9.7%)
Hyponatremia [Hyponatremia includes hyponatremia and blood sodium decreased.] | 17 (6.4%) | 3 (1.1%)
Skin and subcutaneous tissue disorders
Rash [Rash includes rash, rash erythematous, and rash generalized.] | 11 (4.1%) | 5 (1.9%)

Less Common Adverse Reactions Reported in Trial 1

The following selected adverse reaction was reported in RECARBRIO-treated subjects at a rate of less than 4%:

Blood and lymphatic system disorders: thrombocytopenia

In Trials 2 and 3, adverse reactions occurred during the protocol specified follow-up period, which was IV therapy plus 14 days following completion of therapy, in 39% (85/216) of patients receiving imipenem 500 mg/cilastatin 500 mg plus relebactam 250 mg and 36% (77/214) of patients receiving imipenem 500 mg/cilastatin 500 mg. Table 6 lists the most common adverse reactions occurring in ≥1% of patients receiving imipenem 500 mg/cilastatin 500 mg plus relebactam 250 mg or imipenem 500 mg/cilastatin 500 mg in Trials 2 and 3.

Table 6: Adverse Reactions Occurring in Greater Than or Equal to 1% of cUTI and cIAI Adult Patients Receiving Imipenem/Cilastatin plus Relebactam 250 mg or Imipenem/Cilastatin in Trials 2 and 3
Adverse Reaction | Imipenem/Cilastatin and Relebactam 250 mg [Imipenem/Cilastatin (500 mg/500 mg) + Relebactam (250 mg), IV every 6 hours.] (N=216) N (%) | IMI + Placebo [Imipenem/Cilastatin (500 mg/500 mg) + Placebo, IV every 6 hours.] (N=214) N (%)
Blood and lymphatic system disorders
Anemia [Anemia includes anemia and hemoglobin decreased.] | 2 (1%) | 4 (2%)
Gastrointestinal disorders
Diarrhea | 12 (6%) | 9 (4%)
Nausea | 12 (6%) | 12 (6%)
Vomiting | 7 (3%) | 4 (2%)
General disorders and administration site conditions
Phlebitis/Infusion site reactions [Infusion site reactions include infusion site phlebitis, infusion site erythema, and infusion site pain.] | 5 (2%) | 3 (1%)
Pyrexia | 5 (2%) | 3 (1%)
Laboratory Investigations
Alanine aminotransferase increased | 7 (3%) | 4 (2%)
Aspartate aminotransferase increased | 6 (3%) | 3 (1%)
Lipase increased | 3 (1%) | 4 (2%)
Blood creatinine increased | 1 (<1%) | 3 (1%)
Nervous system disorders
Headache | 9 (4%) | 5 (2%)
Central nervous system adverse reactions [Central nervous system adverse reactions include agitation, apathy, confusional states, delirium, disorientation, slow speech, and somnolence.] | 2 (1%) | 5 (2%)
Vascular disorders
Hypertension [Hypertension includes hypertension and blood pressure increased.] | 4 (2%) | 6 (3%)

Other Adverse Reactions Associated with Imipenem/Cilastatin

Adverse reactions reported with imipenem/cilastatin, a component of RECARBRIO, in clinical studies or during post-marketing experience are listed below. These adverse reactions are not listed above for patients treated with RECARBRIO in Trial 1 or imipenem 500 mg/cilastatin 500 mg plus relebactam 250 mg in Trials 2 and 3.

Blood and Lymphatic System Disorders: agranulocytosis, increased eosinophils, hemolytic anemia

Nervous System Disorders: seizure

Hepatobiliary Disorders: hepatic failure, jaundice

Laboratory Investigations: blood lactate dehydrogenase increased, Coombs test positive, eosinophil count increased.

Pediatric Patients

Clinical Trial Experience in Pediatric Patients with HABP/VABP, cUTI and cIAI

RECARBRIO was evaluated in an open-label, randomized, active-controlled, multi-dose, phase 2/3 clinical trial (Trial 4) in pediatric patients from birth to less than 18 years of age with HABP/VABP, cUTI or cIAI [see Clinical Studies (14.3)]. A total of 85 patients were treated with RECARBRIO and 28 were treated with a comparator agent (investigator's choice from a specified list of comparators). RECARBRIO was administered intravenously as a weight-based dose of 37.5 mg/kg (imipenem 15 mg/kg, cilastatin 15 mg/kg, and relebactam 7.5 mg/kg) every 6 hours or 8 hours, or a fixed-dose of 1.25 grams (imipenem 500 mg, cilastatin 500 mg, and relebactam 250 mg) every 6 hours. In Trial 4, adverse reactions were comparable to those observed in adults. No patient died in either intervention group in the study through Day 28. The most common adverse reactions occurring in greater than 3% of pediatric patients receiving RECARBRIO were vomiting (15%), diarrhea (9%), nausea (7%), headache (6%), phlebitis/infusion site reactions (including phlebitis, infusion site phlebitis, infusion site extravasation, medical device site dermatitis; 5%), and rash (including rash, rash erythematous, rash maculopapular; 4%).

7 DRUG INTERACTIONS

7.1 Ganciclovir

Generalized seizures have been reported in patients who received ganciclovir concomitantly with imipenem/cilastatin, a component of RECARBRIO. Ganciclovir should not be used concomitantly with RECARBRIO unless the potential benefits outweigh the risks.

7.2 Valproic Acid

Based on case reports in the literature concomitant use of carbapenems, including imipenem/cilastatin, components of RECARBRIO, with valproic acid or divalproex sodium may decrease valproic acid concentrations which may increase the risk of breakthrough seizures [see Warnings and Precautions (5.3)]. Although the mechanism of this interaction is unknown, data from in vitro and animal studies suggest that carbapenems may inhibit the hydrolysis of valproic acid's glucuronide metabolite (VPA-g) back to valproic acid, thus decreasing the serum concentrations of valproic acid. Avoid concomitant use of RECARBRIO with valproic acid or divalproex sodium. Consider alternative antibacterials other than carbapenems to treat infections in patients whose seizures are well controlled on valproic acid or divalproex sodium.

8 USE IN SPECIFIC POPULATIONS

8.1 Pregnancy

Risk Summary

Embryonic loss was observed in monkeys treated with imipenem/cilastatin, and fetal abnormalities were observed in relebactam-treated mice; therefore, advise pregnant women of the potential risks to pregnancy and the fetus. There are insufficient human data to establish whether there is a drug-associated risk for major birth defects, miscarriage, or adverse maternal or fetal outcomes with RECARBRIO, imipenem, cilastatin, or relebactam in pregnant women.

Developmental toxicity studies with imipenem and cilastatin (alone or in combination) administered parenterally during organogenesis to mice, rats, rabbits, and monkeys at doses 1 to 5 times the maximum recommended human dose (MRHD of imipenem 500 mg/cilastatin 500 mg every 6 hours for total daily doses of imipenem 2000 mg/cilastatin 2000 mg) based on body surface area comparison, showed no drug-induced fetal malformations. Embryofetal development studies with imipenem/cilastatin administered to cynomolgus monkeys at doses similar to the MRHD (based on body surface area comparison) showed an increase in embryonic loss. In an embryofetal study, parental administration of relebactam to pregnant mice during the period of organogenesis was associated with a non-dose responsive increase in the litter incidence of cleft palate at a plasma relebactam exposure approximately equal to the human exposure at the MRHD (250 mg every 6 hours for a daily dose of 1000 mg) and an increased percent litter incidence of total skeletal malformations at a plasma exposure approximately 6 times the human exposure at the MRHD. Reproductive studies with relebactam administered parenterally to pregnant rats and rabbits during the period of organogenesis at plasma exposures up to 7 and 24 times, respectively, the plasma exposure in humans at the MRHD showed no adverse effects on pregnancy or embryofetal development. Relebactam administered to rats during gestation through lactation was not associated with fetal toxicity, developmental delays, or impaired reproduction in first generation offspring at plasma exposures equivalent to 8 times the human exposure at the MRHD (see Data).

The background risk of major birth defects and miscarriage for the indicated populations is unknown. All pregnancies have a background risk of birth defect, loss, or other adverse outcomes. The estimated background risk of major birth defects is 2 to 4% and miscarriage is 15 to 20% of clinically recognized pregnancies within the U.S. general population.

Data

Animal Data

Imipenem and Cilastatin

Reproductive toxicity studies with imipenem and cilastatin (alone or in combination) administered parenterally to mice, rats, and rabbits showed no evidence of effects on embryofetal (mice, rats, and rabbits) or pre/postnatal (rats) development. In embryofetal development studies, imipenem was administered intravenously to rats (gestation days (GD) 7 to 17), and rabbits (GD 6 to 18), at doses up to 900 and 60 mg/kg/day, respectively, approximately 4 and 0.6 times the MRHD (based on body surface area comparison). Cilastatin was administered subcutaneously to rats (GD 6 to 17) and intravenously to rabbits (GD 6 to 18) at doses up to 1000 and 300 mg/kg/day, respectively, approximately 5 and 3 times the MRHD (based on body surface area comparison). Imipenem/cilastatin was administered intravenously to mice at doses up to 320 mg/kg/day (GD 6 to 15) which is approximately equivalent to the MRHD based on body surface area comparison, and to rats at intravenous doses up to 80 mg/kg/day and a subcutaneous dose of 320 mg/kg/day (GD 6 to 17). In a separate pre-postnatal development study, rats were administered subcutaneous imipenem/cilastatin at doses up to 320 mg/kg/day (GD 15 to day 21 postpartum). The subcutaneous dose of 320 mg/kg/day in rats is approximately double the MRHD based on body surface area comparison.

Imipenem/cilastatin administered intravenously to pregnant cynomolgus monkeys during organogenesis (GD 21 to 50) at 100 mg/kg/day, a dose approximately equivalent to the MRHD (based on body surface area comparison), at an infusion rate mimicking human clinical use was not associated with fetal malformations, but there was an increase in embryonic loss relative to controls. Imipenem/cilastatin administered to pregnant cynomolgus monkeys during organogenesis at 40 mg/kg/day by bolus intravenous injection caused significant maternal toxicity including death and embryofetal loss.

Relebactam

In an embryofetal development study in pregnant mice, relebactam administered subcutaneously in doses of 80, 200, and 450 mg/kg/day during the period of organogenesis (GD 6 to 17) was not associated with maternal toxicity at doses up to 450 mg/kg/day. However, although individual skeletal malformations appeared only as single occurrences in the high dose group, the percent litter incidence of total skeletal malformations (skull and vertebral) was increased in the high-dose group (21% litter incidence) compared to the concurrent control value (5.3% litter incidence). The plasma relebactam exposure for the high dose associated with increased skeletal malformations was approximately 6 times greater than the human plasma exposure at the MRHD based on AUC comparison. Also, mice receiving the lowest administered dose of relebactam, 80 mg/kg/day, exhibited a higher percent litter incidence (15% litter incidence) of cleft palate (a rare malformation in mice) compared to the concurrent control value (0% litter incidence) and historical control values (up to 11% litter incidence). This finding did not increase in a dose-dependent manner with percent litter incidences of 0% and 5.3% in the mid- and high-dose groups respectively. The plasma AUC exposure for the low dose of relebactam associated with increased cleft palate was approximately equivalent to the human plasma AUC at the MRHD. In embryofetal development studies in rats and rabbits, intravenous relebactam was administered to rats in doses of 50, 150, and 450 mg/kg/day and rabbits in doses of 35, 275, and 450 mg/kg/day. In these studies, relebactam administered during the period of organogenesis to pregnant rats (GD 6 to 20) and rabbits (GD 7 to 20) was not associated with maternal or embryofetal toxicity at doses up to 450 mg/kg/day corresponding to plasma AUC exposures of approximately 7 and 24 times, respectively, the human plasma AUC at the MRHD.

In a pre-postnatal development study, relebactam administered intravenously in doses of 65, 200, and 450 mg/kg/day to rats from GD 6 to lactation day (LD) 20 produced no maternal toxicity and did not impair the physical and behavioral development or reproduction in first generation offspring at doses up to 450 mg/kg/day corresponding to a plasma AUC exposure of approximately 8 times the plasma AUC exposure in humans at the MRHD.

Studies in pregnant rats and rabbits showed that relebactam is transferred to the fetus through the placenta, with fetal plasma concentrations up to 5% to 6% of maternal concentrations observed on GD 20.

8.2 Lactation

Risk Summary

There are insufficient data on the presence of imipenem/cilastatin and relebactam in human milk, and no data on the effects on the breastfed child, or the effects on milk production. Relebactam is present in the milk of lactating rats (see Data).

The developmental and health benefits of breastfeeding should be considered along with the mother's clinical need for RECARBRIO and any potential adverse effects on the breastfed child from RECARBRIO or from the underlying maternal condition.

Data

Relebactam administered intravenously to lactating rats at a dose of 450 mg/kg/day (GD 6 to LD 14), was excreted into the milk with concentrations of approximately 5% that of maternal plasma concentrations.

8.4 Pediatric Use

The safety and effectiveness of RECARBRIO for the treatment of HABP/VABP, and for the treatment of cUTI and cIAI in patients who have limited or no alternative treatment options have been established in pediatric patients weighing at least 2 kg. Use of RECARBRIO in pediatric patients is supported by evidence from an adequate and well-controlled trial of RECARBRIO in adults with HABP/VABP, controlled trials in adults with cUTI and cIAI, and additional pharmacokinetic, safety, and efficacy data from pediatric trials [see Clinical Pharmacology (12.3) and Clinical Studies (14.1, 14.2 and 14.3)].

The safety profile of RECARBRIO in pediatric patients from the pediatric trials was comparable to that in adults treated with RECARBRIO [see Adverse Reactions (6.1)].

RECARBRIO is not recommended in pediatric patients less than 37 weeks post-menstrual age (gestational age at birth plus post-natal age) or weighing less than 30 kg with renal impairment.

The safety and effectiveness of RECARBRIO for the treatment of HABP/VABP, cUTI or cIAI have not been established in pediatric patients weighing less than 2 kg.

8.5 Geriatric Use

Of the 266 patients treated with RECARBRIO in Trial 1, 113 (42.5%) were 65 years of age or older, including 55 (20.7%) patients 75 years of age and older. Of the 216 patients treated with imipenem/cilastatin plus relebactam 250 mg in Trials 2 and 3, 67 (31.0%) were 65 years of age or older, including 25 (11.6%) patients 75 years of age and older. No overall differences in safety or effectiveness were observed between these patients and younger patients, and other reported clinical experience has not identified differences in responses between the elderly and younger patients, but greater sensitivity of some older individuals cannot be ruled out.

RECARBRIO is known to be substantially excreted by the kidney, and the risk of adverse reactions to this drug may be greater in patients with impaired renal function. Because elderly patients are more likely to have decreased renal function, care should be taken in dose selection, and it may be useful to monitor renal function. No dosage adjustment is required based on age. Dosage adjustment for elderly patients should be based on renal function [see Dosage and Administration (2.2) and Clinical Pharmacology (12.3)].

8.6 Renal Impairment

Reduce RECARBRIO dosage in adult patients with a CLcr less than 90 mL/min and in pediatric patients weighing at least 30 kg with an eGFR less than 90 mL/min/1.73 m^2 [see Dosage and Administration (2.3, 2.4) and Clinical Pharmacology (12.3)]. RECARBRIO is not recommended in pediatric patients weighing less than 30 kg with renal impairment.

10 OVERDOSAGE

In the event of overdose, discontinue RECARBRIO, treat symptomatically, and institute general supportive treatment. Imipenem, cilastatin, and relebactam can be removed by hemodialysis [see Clinical Pharmacology (12.3)]. No clinical information is available on the use of hemodialysis to treat overdosage.

11 DESCRIPTION

RECARBRIO (imipenem, cilastatin, and relebactam) for injection is an antibacterial combination product consisting of imipenem, a carbapenem antibacterial drug, cilastatin, a renal dehydropeptidase inhibitor, and relebactam, a diazabicyclooctane beta-lactamase inhibitor, for intravenous administration.

Imipenem

Imipenem is a beta lactam antibacterial drug. Imipenem (N-formimidoylthienamycin monohydrate) is a crystalline derivative of thienamycin, which is produced by Streptomyces cattleya. The chemical name is (5R,6S)-3-[[2-(formimidoylamino)ethyl]thio]-6-[(R)-1-hydroxyethyl]-7-oxo-1-azabicyclo[3.2.0]hept-2-ene-2-carboxylic acid monohydrate. It is an off-white, non-hygroscopic crystalline compound, sparingly soluble in water. The empirical formula is C12H17N3O4S∙H2O and the molecular weight is 317.37.

Figure 1: Chemical structure of imipenem

Cilastatin

Cilastatin sodium is the sodium salt of a derivatized heptenoic acid. The chemical name is sodium (Z)-7-[[(R)-2-amino-2-carboxyethyl]thio]-2-[(S)-2,2-dimethylcyclopropanecarboxamido]-2-heptenoate. It is an off-white to white, hygroscopic, amorphous compound, very soluble in water. The empirical formula is C16H25N2NaO5S and the molecular weight is 380.44.

Figure 2: Chemical structure of cilastatin sodium

Relebactam

Relebactam is a beta-lactamase inhibitor. It is a crystalline monohydrate. The chemical name is (1R,2S,5R)-7-oxo-2-(piperidin-1-ium-4-ylcarbamoyl)-1,6-diazabicyclo[3.2.1]octan-6-yl sulfate hydrate. It is a white to off-white powder, soluble in water. The empirical formula is C12H20N4O6S∙H2O and the molecular weight is 366.39.

Figure 3: Chemical structure of relebactam

RECARBRIO is supplied as a white to light yellow sterile powder for constitution in a single-dose vial containing 500 mg imipenem (equivalent to 530 mg imipenem monohydrate), 500 mg cilastatin (equivalent to 531 mg cilastatin sodium), and 250 mg relebactam (equivalent to 263 mg relebactam monohydrate). Each vial of RECARBRIO is buffered with 20 mg sodium bicarbonate to provide solutions in the pH range of 6.5 to 7.6. The total sodium content of the mixture in the vial is 37.5 mg (1.6 mEq). Solutions of RECARBRIO range from colorless to yellow. Variations of color within this range do not affect the potency of the product.

12 CLINICAL PHARMACOLOGY

12.1 Mechanism of Action

RECARBRIO is an antibacterial drug [see Microbiology (12.4)].

12.2 Pharmacodynamics

For imipenem, the % time of dosing interval that unbound plasma concentrations of imipenem exceed the imipenem/relebactam minimum inhibitory concentration (MIC) (%fT>MIC) against the infecting organism best correlates with antibacterial activity in animal and in vitro models of infection. For relebactam the ratio of the 24-hour unbound plasma relebactam AUC to imipenem/relebactam MIC (fAUC0–24hr/MIC) best predicts the activity of relebactam in animal and in vitro models of infection.

Cardiac Electrophysiology

At a dose 4.6 times the recommended dose, relebactam does not prolong the QTc interval to a clinically relevant extent.

12.3 Pharmacokinetics

The steady-state pharmacokinetic parameters of imipenem, cilastatin, and relebactam in healthy adults with normal renal function (CLcr 90 mL/min or greater), after multiple 30-minute intravenous infusions of RECARBRIO administered every 6 hours are summarized in Table 7. Pharmacokinetic parameters were similar for single and multiple dose administration due to minimal accumulation. Pharmacokinetic parameters in pediatric patients are described in Table 9.

Adult Patients

The steady-state pharmacokinetic parameters of imipenem and relebactam in patients with active bacterial infection with CLcr 90 mL/min or greater following administration of the recommended dosage are summarized in Table 7.

Table 7: Population Pharmacokinetic Model-Based Steady State Mean (±SD) Plasma Pharmacokinetic Parameters of Imipenem and Relebactam After Multiple 30 Minute Intravenous Infusions [Imipenem/cilastatin and relebactam were administered either as separate infusions given concurrently or as the fixed dose combination (RECARBRIO).] of Imipenem 500 mg/Cilastatin 500 mg and Relebactam 250 mg Every 6 Hours in Adult Patients with CLcr 90 mL/min or Greater
 | PK Parameters | cUTI/cIAI Patients | HABP/VABP Patients
Imipenem | AUC0-24hr (µM-hr) | 570.6 (253.3) | 771 (342.3)
 | Cmax (µM) | 116.1 (52.4) | 122.7 (56.8)
 | CL (L/hr) | 14 (6.1) | 10.4 (4.5)
Relebactam | AUC0-24hr (µM-hr) | 415.8 (212.6) | 692.9 (354.3)
 | Cmax (µM) | 62.1 (24.7) | 80 (33.3)
 | CL (L/hr) | 8.7 (4.5) | 5.2 (2.7)
AUC0-24hr=area under the concentration time curve from 0 to 24 hours
Cmax=maximum concentration
CL=plasma clearance

Distribution

The binding of imipenem and cilastatin to human plasma proteins is approximately 20% and 40%, respectively. The binding of relebactam to human plasma proteins is approximately 22% and is independent of concentration at a range of 5 to 50 µM.

The penetration of imipenem and relebactam into pulmonary epithelial lining fluid is similar, with concentrations around 55% and 54% of unbound plasma concentrations of imipenem and relebactam, respectively.

The steady-state volume of distribution of imipenem, cilastatin, and relebactam is 24.3 L, 13.8 L, and 19.0 L, respectively, in subjects following multiple doses infused over 30 minutes every 6 hours.

Elimination

Imipenem and relebactam are eliminated from the body by the kidneys with a mean (±SD) half-life of 1 (±0.5) hour and 1.2 (±0.7) hours, respectively.

Metabolism

Imipenem, when administered alone, is metabolized in the kidneys by dehydropeptidase, resulting in low levels of imipenem recovered in human urine. Cilastatin, an inhibitor of this enzyme, effectively prevents renal metabolism so that when imipenem and cilastatin are given concomitantly, adequate concentrations of imipenem are achieved in the urine to enable antibacterial activity.

Relebactam is minimally metabolized. Unchanged relebactam was the only drug-related component detected in human plasma.

Excretion

Imipenem, cilastatin, and relebactam are mainly excreted by the kidneys.

Following multiple-dose administration of imipenem 500 mg, cilastatin 500 mg, and relebactam 250 mg to healthy male subjects, approximately 63% of the administered imipenem dose, and 77% of the administered cilastatin dose are recovered as unchanged parent drugs in the urine. The renal excretion of imipenem and cilastatin involves both glomerular filtration and active tubular secretion. Greater than 90% of the administered relebactam dose was excreted unchanged in human urine. The unbound renal clearance of relebactam is greater than the glomerular filtration rate, suggesting that in addition to glomerular filtration, active tubular secretion is involved in the renal elimination, accounting for ~30% of the total clearance.

Specific Populations

No clinically significant differences in the pharmacokinetics of imipenem, cilastatin, or relebactam were observed based on age, gender, or race/ethnicity.

Patients with Renal Impairment

In a single-dose trial evaluating the effect of renal impairment on the PK of relebactam 125 mg co-infused with imipenem/cilastatin 250 mg (half the recommended dose in patients with normal renal function), mean AUC was higher in subjects with CLcr 60-89, 30-59, and 15-29 mL/min, respectively, compared to healthy subjects with CLcr 90 mL/min or greater (Table 8). In subjects with end stage renal disease (ESRD) on hemodialysis, imipenem, cilastatin, and relebactam are removed by hemodialysis, with extraction coefficients of 66% to 87% for imipenem, 46% to 56% for cilastatin, and 67% to 87% for relebactam.

Table 8: Mean AUC Increase in Adult Subjects with Renal Impairment Compared to Subjects with CLcr 90 mL/min or Greater
Estimated CLcr (mL/min) | Imipenem | Cilastatin | Relebactam
60 to 89 | 1.1-fold | 1.2-fold | 1.2-fold
30 to 59 | 1.7-fold | 2.0-fold | 2.2-fold
15 to 29 | 2.6-fold | 5.5-fold | 4.7-fold

To maintain systemic exposures similar to patients with normal renal function, dose adjustment is recommended for patients with renal impairment [see Dosage and Administration (2.3)]. ESRD patients on hemodialysis should receive RECARBRIO after hemodialysis session [see Dosage and Administration (2.3)].

Patients with Hepatic Impairment

Imipenem, cilastatin, and relebactam are primarily cleared renally; therefore, hepatic impairment is not likely to have any effect on RECARBRIO exposures.

Pediatric Patients

The pharmacokinetics of imipenem and relebactam were evaluated in two clinical studies (N = 131) in pediatric patients from birth (includes pediatric patients at least 37 weeks post-menstrual age) to less than 18 years of age who received RECARBRIO. Steady-state PK parameters of imipenem and relebactam in patients with HABP/VABP, cUTI, or cIAI (eGFR ≥90 mL/min/1.73 m²) following recommended pediatric dosing [see Dosage and Administration (2.2, 2.4)] are in Table 9 below.

Table 9: Population Pharmacokinetic Model Based Steady-State Mean (±SD) Plasma Pharmacokinetic Parameters Following Administration of the Recommended Dosing Regimens of RECARBRIO in HABP/VABP, cUTI or cIAI Pediatric Patients (Birth [Pediatric patients from birth (includes pediatric patients at least 37 weeks post-menstrual age)] to <18 Years) with Normal Renal Function
Body Weight (WT) Age |  | Imipenem |  | Relebactam
Body Weight (WT) Age |  | AUC0-24h (μM.hr) | Cmax (μM) | CL/WT (L/hr/kg) | AUC0-24h (μM.hr) | Cmax (μM) | CL/WT (L/hr/kg)
≥30 kg | <18 years | 702 (272) | 119 (27.80) | 0.246 (0.0636) | 461 (207) | 63.2 (17.20) | 0.165 (0.0475)
<30 kg | ≥3 months to <18 years | 739 (203) | 105 (15.90) | 0.289 (0.0699) | 516 (257) | 58.6 (13.60) | 0.193 (0.0634)
<30 kg | Birth* to <3 months | 765 (165) | 112 (14.80) | 0.205 (0.0413) | 592 (263) | 61.2 (13.20) | 0.127 (0.0449)
AUC0-24h=area under the plasma concentration time curve from time 0 to 24 hours
Cmax=maximum concentration
CL=clearance

Drug Interaction Studies

Clinical Studies

No drug-drug interaction was observed among imipenem, cilastatin, and relebactam in a clinical study in healthy subjects.

No clinically significant differences in the pharmacokinetics of imipenem or relebactam were observed when RECARBRIO was used concomitantly with probenecid (Organic Anion Transporter 3 (OAT3) inhibitor).

In Vitro Studies

CYP Enzymes

Relebactam does not inhibit CYP1A2, CYP2B6, CYP2C8, CYP2C9, CYP2C19, CYP2D6, or CYP3A4 or induce CYP1A2, CYP2B6, or CYP3A4 in human hepatocytes.

Transporter Systems

Relebactam does not inhibit OATP1B1, OATP1B3, OAT1, OAT3, OCT2, P-gp, BCRP, MATE1, MATE2K, or BSEP.

Relebactam is not a substrate of OAT1, OCT2, P-gp, BCRP, MRP2, or MRP4 transporters, but is a substrate of OAT3, OAT4, MATE1, and MATE2K transporters.

The following antibacterial and antifungal drugs (piperacillin/tazobactam, ciprofloxacin, fluconazole, ampicillin, levofloxacin, metronidazole, vancomycin, linezolid, daptomycin, and cefazolin) did not significantly inhibit OAT3-mediated relebactam uptake.

12.4 Microbiology

Mechanism of Action

RECARBRIO is a combination of imipenem/cilastatin and relebactam. Imipenem is a penem antibacterial drug, cilastatin sodium is a renal dehydropeptidase inhibitor, and relebactam is a beta-lactamase inhibitor. Cilastatin limits the renal metabolism of imipenem and does not have antibacterial activity. The bactericidal activity of imipenem results from binding to PBP 2 and PBP 1B in Enterobacterales and Pseudomonas aeruginosa and the subsequent inhibition of penicillin binding proteins (PBPs). Inhibition of PBPs leads to the disruption of bacterial cell wall synthesis. Imipenem is stable in the presence of some beta-lactamases. Relebactam has no intrinsic antibacterial activity. Relebactam protects imipenem from degradation by certain serine beta-lactamases such as Sulfhydryl Variable (SHV), Temoneira (TEM), Cefotaximase-Munich (CTX-M), Enterobacter cloacae P99 (P99), Pseudomonas-derived cephalosporinase (PDC, AmpC-type), and Klebsiella-pneumoniae carbapenemase (KPC).

Resistance

Clinical isolates may produce multiple beta-lactamases, express varying levels of beta-lactamases, have amino acid sequence variations, or have other resistance mechanisms that have not yet been identified. Culture and susceptibility information and local epidemiology should be considered in selecting or modifying antibacterial therapy.

Mechanisms of beta lactam resistance in gram-negative organisms include the production of beta-lactamases, up-regulation of efflux pumps, and loss of outer membrane porins. Imipenem/relebactam retains activity in the presence of the tested efflux pumps. Imipenem/relebactam has shown activity against some isolates of P. aeruginosa and Enterobacterales that produce relebactam-susceptible beta-lactamases concomitant with loss of entry porins. Imipenem/relebactam is not active against most isolates containing metallo-betalactamases- (MBLs), some oxacillinases with carbapenemase activity, as well as certain alleles of GES.

Imipenem/relebactam demonstrated in vitro activity against some Enterobacterales isolates genotypically characterized for some beta-lactamases and extended-spectrum beta-lactamases (ESBLs) of the following groups: KPC, TEM, SHV, CTX-M, CMY, DHA, and ACT/MIR. Many of the Enterobacterales isolates that were not susceptible to imipenem-relebactam were genotypically characterized and the genes encoding MBLs or certain oxacillinases were present.

Imipenem/relebactam demonstrated in vitro activity against genotypically characterized P. aeruginosa isolates containing certain known resistance factors: some chromosomal PDC alleles with ESBLs, and some with loss of outer membrane porin (OprD) with or without co-expression of up-regulated efflux pumps (MexAB, MexCD, MexJK, and MexXY). Genotypically characterized P. aeruginosa isolates that were not susceptible to imipenem/relebactam encoded some MBL, KPC, PER, GES, VEB, and PDC alleles.

Methicillin-resistant staphylococci should be considered resistant to imipenem. Imipenem is inactive in vitro against Enterococcus faecium, Stenotrophomonas maltophilia, and some isolates of Burkholderia cepacia.

No cross-resistance with other classes of antimicrobials has been identified. Some isolates resistant to carbapenems (including imipenem) and to cephalosporins may be susceptible to RECARBRIO.

Interaction with Other Antimicrobials

In vitro studies have demonstrated no antagonism between imipenem/relebactam and amikacin, azithromycin, aztreonam, colistin, gentamicin, levofloxacin, linezolid, tigecycline, tobramycin, or vancomycin.

Activity against Imipenem-Nonsusceptible Bacteria in Animal Infection Models

Relebactam restored activity of imipenem/cilastatin in animal models of infection (e.g., mouse disseminated infection, mouse thigh infection, and mouse pulmonary infection) caused by imipenem-nonsusceptible KPC-producing Enterobacterales and imipenem-nonsusceptible P. aeruginosa (imipenem-nonsusceptible due to production of chromosomal PDC and loss of OprD porin).

Antimicrobial Activity

RECARBRIO has been shown to be active against most isolates of the following bacteria, both in vitro and in clinical infections [see Indications and Usage (1.1) and (1.2)].

Hospital-acquired Bacterial Pneumonia and Ventilator-associated Bacterial Pneumonia (HABP/VABP)

Aerobic Bacteria
  Gram-negative Bacteria
    - Acinetobacter calcoaceticus-baumannii complex
    - Enterobacter cloacae
    - Escherichia coli
    - Haemophilus influenzae
    - Klebsiella aerogenes
    - Klebsiella oxytoca
    - Klebsiella pneumoniae
    - Pseudomonas aeruginosa
    - Serratia marcescens

Complicated Urinary Tract Infections (cUTI)

Aerobic Bacteria
  Gram-negative Bacteria
    - Klebsiella aerogenes
    - Enterobacter cloacae
    - Escherichia coli
    - Klebsiella pneumoniae
    - Pseudomonas aeruginosa

Complicated Intra-abdominal Infections (cIAI)

Aerobic Bacteria
  Gram-negative Bacteria
    - Citrobacter freundii
    - Klebsiella aerogenes
    - Enterobacter cloacae
    - Escherichia coli
    - Klebsiella oxytoca
    - Klebsiella pneumoniae
    - Pseudomonas aeruginosa
Anaerobic Bacteria
  Gram-negative Bacteria
    - Bacteroides caccae
    - Bacteroides fragilis
    - Bacteroides ovatus
    - Bacteroides stercoris
    - Bacteroides thetaiotaomicron
    - Bacteroides uniformis
    - Bacteroides vulgatus
    - Fusobacterium nucleatum
    - Parabacteroides distasonis

The following in vitro data are available, but their clinical significance is unknown. At least 90% of the following bacteria exhibit an in vitro MIC less than or equal to the susceptible breakpoint for RECARBRIO against isolates of similar genus or organism group. However, the efficacy of RECARBRIO in treating clinical infections due to these bacteria has not been established in adequate and well-controlled clinical trials.

Aerobic Bacteria
  Gram-positive Bacteria
    - Enterococcus faecalis
    - Methicillin-susceptible Staphylococcus aureus
    - Streptococcus anginosus
    - Streptococcus constellatus
    - Streptococcus pneumoniae
  Gram-negative Bacteria
    - Citrobacter koseri
    - Enterobacter asburiae
Anaerobic Bacteria
  Gram-positive Bacteria
    - Eggerthella lenta
    - Parvimonas micra
    - Peptoniphilus harei
    - Peptostreptococcus anaerobius
  Gram-negative Bacteria
    - Fusobacterium necrophorum
    - Fusobacterium varium
    - Parabacteroides goldsteinii
    - Parabacteroides merdae
    - Prevotella bivia
    - Veillonella parvula

Susceptibility Test Methods

For specific information regarding susceptibility testing methods, interpretive criteria, and associated test methods and quality control standards recognized by FDA for RECARBRIO, please see: https://www.fda.gov/STIC.

13 NONCLINICAL TOXICOLOGY

13.1 Carcinogenesis, Mutagenesis, Impairment of Fertility

Carcinogenesis

Carcinogenicity studies with imipenem/cilastatin or relebactam have not been conducted.

Mutagenesis

Genotoxicity studies were performed in a variety of bacterial and mammalian tests in vivo and in vitro. None of these tests showed any evidence of genetic damage.

The tests conducted with imipenem, cilastatin, or imipenem/cilastatin included: V79 mammalian cell mutagenesis assay (imipenem, cilastatin), Ames test (imipenem, cilastatin), unscheduled DNA synthesis assay (imipenem/cilastatin), and in vivo mouse cytogenetics test (imipenem/cilastatin).

The tests conducted with relebactam included: Ames test, in vitro chromosomal aberration in Chinese Hamsters Ovary (CHO) cells, and in vivo rat micronucleus test.

Impairment of Fertility

No adverse effects on fertility, reproductive performance, fetal viability, growth or postnatal development were observed in male and female rats given imipenem/cilastatin at intravenous doses up to 80 mg/kg/day and at a subcutaneous dose of 320 mg/kg/day. In rats, a dose of 320 mg/kg was approximately double the MRHD based on body surface area. Slight decreases in live fetal body weight were restricted to the highest dosage level.

In fertility studies, relebactam was administered in intravenous doses of 50, 150, and 450 mg/kg/day to male rats beginning 15 days before mating, through mating, and for an additional 3 weeks and to female rats beginning 15 days before mating, through mating, and until gestation day (GD) 7. Relebactam did not impair fertility, reproductive performance or spermatogenesis in males or fertility, reproductive performance, or early embryonic development in females at doses up to 450 mg/kg/day corresponding to plasma AUC exposures of approximately 8 times in males and 7 times in females the plasma AUC exposure in humans at the MRHD.

13.2 Animal Toxicology and/or Pharmacology

Relebactam given as a single entity caused renal tubular degeneration in monkeys at AUC exposure 7-fold the human AUC exposure at the MRHD. Renal tubular degeneration was shown to be reversible after dose discontinuation. There was no evidence of nephrotoxicity at AUC exposures less than or equal to 3-fold the human AUC exposure at the MRHD.

14 CLINICAL STUDIES

14.1 Hospital-acquired Bacterial Pneumonia and Ventilator-associated Bacterial Pneumonia in Adult Patients

A total of 535 hospitalized adults with HABP/VABP were randomized and received trial medications in a multinational, double-blind trial (Trial 1, NCT02493764) comparing RECARBRIO 1.25 grams (imipenem 500 mg/cilastatin 500 mg/relebactam 250 mg) intravenously every 6 hours to piperacillin and tazobactam (4.5 grams) for 7 to 14 days of therapy.

The modified intent-to-treat (MITT) population, which included all randomized patients who received at least one dose of trial treatment and did not have only gram-positive cocci on Gram stain of the baseline lower respiratory tract (LRT) specimen included 531 patients; the mean age was 60 and 43% were 65 years of age or older. The majority of patients were men (69%), white (78%), and from Europe (61%). The mean APACHE II score was 15 and 47% of the population had an APACHE II score of ≥15. At randomization, 66% of patients were admitted to the ICU, 77% had been in the hospital for ≥5 days, and 48% had a creatinine clearance of <90 mL/min. Concurrent bacteremia was present at baseline in 5.8% of patients.

Table 10 presents the incidence of all-cause mortality through Day 28 and clinical response at the early follow-up (EFU) visit (7 to 14 days after the end of therapy) in the MITT population. Overall results are presented along with subgroup results by pneumonia diagnosis.

Table 10: Day 28 All-Cause Mortality and Clinical Response Rates at EFU from Trial 1 of Hospital-acquired Bacterial Pneumonia and Ventilator-associated Bacterial Pneumonia (HABP/VABP) (MITT Population)
 | RECARBRIO |  | Piperacillin/Tazobactam |  | Treatment Difference
 | n/m | (%) | n/m | (%) | % [Treatment differences and 95% confidence intervals are based on Miettinen & Nurminen method.] | (95% CI)
All-Cause Mortality Through Day 28 [n/m = number of subjects with survival status of death or unknown / number of modified intent-to-treat subjects.] , [One subject in the RECARBRIO arm had unknown mortality status at Day 28 which was counted as a death.] | 42/264 | (15.9) | 57/267 | (21.3) | -5.3 | (-11.9, 1.2)
Non-ventilated HABP | 18/142 | (12.7) | 15/131 | (11.5) | 1.2 | (-6.8, 9.1)
Ventilated HABP/VABP | 24/122 | (19.7) | 42/136 | (30.9) | -11.2 | (-21.6, -0.5)
Clinical Response at EFU [n/m = number of subjects with a favorable clinical response / number of modified intent-to-treat subjects.] | 161/264 | (61.0) | 149/267 | (55.8) | 5.0 | (-3.2, 13.2)
Non-ventilated HABP | 95/142 | (66.9) | 87/131 | (66.4) | 0.5 | (-10.7, 11.7)
Ventilated HABP/VABP | 66/122 | (54.1) | 62/136 | (45.6) | 8.5 | (-3.7, 20.5)
EFU = early follow up

In the MITT population, in patients with an APACHE II score <15, Day 28 all-cause mortality rates were 17/139 (12.2%) for RECARBRIO-treated patients and 12/140 (8.6%) for piperacillin/tazobactam-treated patients, clinical cure rates were 90/139 (64.7%) and 98/140 (70%), respectively. In patients with an APACHE II score ≥15, Day 28 all-cause mortality rates were 25/125 (20%) for RECARBRIO-treated patients and 45/127 (35.4%) for piperacillin/tazobactam-treated patients, clinical cure rates were 71/125 (56.8%) and 51/127 (40.2%), respectively.

Per pathogen favorable clinical response at EFU and Day 28 all-cause mortality were assessed in a microbiological modified intention to treat (mMITT) population, which consisted of all randomized MITT subjects who had at least one baseline LRT pathogen that was susceptible to both study treatments (Table 11).

Table 11: Day 28 All-Cause Mortality and Favorable Clinical Response at EFU by Baseline LRT Pathogen from Trial 1 of Hospital-acquired Bacterial Pneumonia and Ventilator-associated Bacterial Pneumonia (HABP/VABP) (mMITT Population)
Baseline LRT Pathogen | Day 28 All-Cause Mortality |  | Clinical Response at EFU
Baseline LRT Pathogen | RECARBRIO n/m [n/m = the number of subjects with survival status of death or unknown within each category / the number of microbiological modified intent-to-treat subjects who have the corresponding baseline pathogen from LRT culture.] (%) | Piperacillin/ Tazobactam n/m (%) | RECARBRIO n/m [n/m = the number of subjects with a favorable clinical response within each category / the number of microbiological modified intent-to-treat subjects who have the corresponding baseline pathogen from LRT culture.] (%) | Piperacillin/ Tazobactam n/m (%)
Acinetobacter calcoaceticus- baumannii complex | 0/5 [Supportive evidence was derived from the imipenem and cilastatin prescribing information.] (0.0) | 1/10 (10.0) | 4/5 (80.0) | 6/10 (60.0)
Enterobacter cloacae | 1/7 (14.3) | 3/16 (18.8) | 6/7 (85.7) | 12/16 (75.0)
Escherichia coli | 5/27(18.5) | 8/33 (24.2) | 16/27 (59.3) | 19/33 (57.6)
Haemophilus influenzae [All H. influenzae isolates were susceptible to imipenem. The susceptible MIC breakpoint for PIP/TAZ is ≤1/4 mcg/mL. At the lowest concentration of PIP/TAZ tested (2/4 mcg/mL) there was no visible growth.] | 2/13 (15.4) | 3/12 (25.0) | 9/13 (69.2) | 8/12 (66.7)
Klebsiella spp [Includes Klebsiella aerogenes, Klebsiella oxytoca, Klebsiella pneumoniae.] | 6/42 (14.3) | 8/41 (19.5) | 25/42 (59.5) | 28/41 (68.3)
Pseudomonas aeruginosa | 7/26 (26.9) | 5/35 (14.3) | 12/26 (46.2) | 20/35 (57.1)
Serratia marcescens | 2/10 (20.0) | 1/4 (25.0) | 7/10 (70.0) | 3/4 (75.0)
LRT = lower respiratory tract
EFU = early follow-up

14.2 Complicated Urinary Tract Infections, including Pyelonephritis and Complicated Intra-abdominal Infections in Adult Patients

The determination of efficacy and safety of RECARBRIO was supported in part by the previous findings of the efficacy and safety of imipenem/cilastatin for the treatment of cUTI and cIAI. The contribution of relebactam to RECARBRIO was primarily established in vitro and in animal models of infection [see Microbiology (12.4)]. Imipenem/cilastatin plus relebactam was studied in cUTI including pyelonephritis (Trial 2, NCT01505634) and cIAI (Trial 3, NCT01506271) in randomized, blinded, active-controlled, multicenter trials. These trials provided only limited efficacy and safety information.

14.3 Hospital-acquired Bacterial Pneumonia and Ventilator-associated Bacterial Pneumonia (HABP/VABP), Complicated Urinary Tract Infections (cUTI), and Complicated Intra-abdominal Infections (cIAI) in Pediatric Patients

The safety and efficacy of RECARBRIO in pediatric patients were investigated in a randomized, active-controlled, open-label trial that enrolled hospitalized patients from birth to less than 18 years of age with HABP/VABP, cUTI, or cIAI (Trial 4, NCT03969901). Eligible patients were randomized in a 3:1 ratio with stratification by age group and infection type to receive IV RECARBRIO or active control (defined as investigator’s choice of specified comparators). Patients with HABP/VABP received IV therapy for 7 to 14 days. Patients with cUTI or cIAI received IV therapy for a minimum of 3 days before an optional switch to oral step-down therapy at the discretion of the investigator to complete a total of the 5 to 14 days of antibacterial therapy.

The modified intention to treat (MITT) population consisted of 113 patients who were randomized and received at least one dose of trial treatment (RECARBRIO, n=85; active control, n=28). In patients treated with RECARBRIO, 49% were male and the median age was 5 years (range 21 days to 17 years). The age groups who received RECARBRIO were as follows: 12 to <18 years (n=10), 6 to <12 years (n=31), 2 to <6 years (n=21), 3 months to <2 years (n=15), and birth to <3 months (n=8). The MITT population included 54 patients (48%) with cUTI, 53 (47%) with cIAI, and 6 (5%) with HABP/VABP. Patients were predominantly white (81%) and from Europe (61%).

The primary objective of the study was to evaluate the safety and tolerability of RECARBRIO. Efficacy assessments were not powered for formal hypothesis testing between treatment groups. For HABP/VABP and cIAI, Table 12 presents the clinical cure rates at early follow-up (EFU, 7 to 14 days after the end of therapy) in the MITT population. For cUTI, Table 13 presents the clinical cure and microbiologic response rates at EFU in the mMITT population, which included all patients with cUTI in the MITT population that had a baseline pathogen isolated. No patient died in either intervention group in the study through Day 28.

Table 12: Clinical Cure Rates at the EFU Visit (7 to 14 Days after End of Therapy) in Pediatric Patients with HABP/VABP or cIAI in Trial 4 (MITT Population)
 | RECARBRIO n/N (%) | Active Control n/N (%)
HABP/VABP | 5/5 (100.0) | 1/1 (100.0)
cIAI | 34/39 (87.2) | 13/14 (92.9)

Table 13: Clinical Cure and Microbiologic Response Rates at the EFU Visit (7 to 14 Days after End of Therapy) in Pediatric Patients with cUTI in Trial 4 (mMITT Population)
 | RECARBRIO n/N (%) | ACTIVE Control n/N (%)
Clinical Cure | 20/30 (66.7) | 7/10 (70.0)
Microbiologic Response | 20/30 (66.7) | 8/10 (80.0)

16 HOW SUPPLIED/STORAGE AND HANDLING

RECARBRIO (imipenem, cilastatin, and relebactam) for injection, 1.25 grams is supplied as a white to light yellow sterile powder for constitution in a single-dose glass vial containing imipenem 500 mg (equivalent to 530 mg imipenem monohydrate), cilastatin 500 mg (equivalent to 531 mg cilastatin sodium), and relebactam 250 mg (equivalent to 263 mg relebactam monohydrate).

The vials are supplied as a single-dose glass vial (NDC 0006-3856-01) and in cartons containing 25 vials (NDC 0006-3856-02).

STORAGE AND HANDLING

Store RECARBRIO vials at 20°C to 25°C (68°F to 77°F), excursions permitted between 15°C to 30°C (between 59°F to 86°F) [see USP Controlled Room Temperature]. Keep vials in the carton.

17 PATIENT COUNSELING INFORMATION

Serious Allergic Reactions

Advise patients, their families, or caregivers that allergic reactions, including serious allergic reactions, could occur that require immediate treatment. Ask them about any previous hypersensitivity reactions to RECARBRIO (imipenem, cilastatin, and relebactam), carbapenems, penicillins, cephalosporins, other beta lactams, or other allergens [see Warnings and Precautions (5.1)].

Seizures and Central Nervous System Reactions

Counsel patients, their families, or caregivers to inform a healthcare provider if they have central nervous system disorders, such as stroke or history of seizures. Seizures have been reported during treatment with imipenem, a component of RECARBRIO, especially when recommended dosages were exceeded and with closely related antibacterial drugs [see Warnings and Precautions (5.2)].

Drug Interaction with Valproic Acid

Counsel patients, their families, or caregivers to inform a healthcare provider if they are taking valproic acid or divalproex sodium. If treatment with RECARBRIO is necessary, supplemental anti-convulsant medication to prevent and/or treat seizures may be needed [see Warnings and Precautions (5.3)].

Potentially Serious Diarrhea

Advise patients, their families, or caregivers that diarrhea is a common problem caused by antibacterial drugs, including RECARBRIO and usually resolves when the drug is discontinued. Sometimes, frequent watery or bloody diarrhea may occur and may be a sign of a more serious intestinal infection that may require treatment. If severe watery or bloody diarrhea develops, tell the patient to contact his or her healthcare provider [see Warnings and Precautions (5.4)].

Antibacterial Resistance

Patients should be counseled that antibacterial drugs, including RECARBRIO, should only be used to treat bacterial infections. They do not treat viral infections (e.g., the common cold). When RECARBRIO is prescribed to treat a bacterial infection, patients should be told that although it is common to feel better early in the course of therapy, the medication should be taken exactly as directed. Skipping doses or not completing the full course of therapy may (1) decrease the effectiveness of the immediate treatment and (2) increase the likelihood that bacteria will develop resistance and will not be treatable by RECARBRIO or other antibacterial drugs in the future [see Warnings and Precautions (5.5)].

Merck Sharp & Dohme LLC
Rahway, NJ 07065, USA

For patent information: www.msd.com/research/patent

Copyright © 2019-2025 Merck & Co., Inc., Rahway, NJ, USA, and its affiliates.
All rights reserved.

uspi-mk7655a-iv-2512r004

PRINCIPAL DISPLAY PANEL - 1.25 g Vial Carton Label

NDC 0006-3856-02

Recarbrio™
(imipenem, cilastatin, and relebactam)
for Injection
1.25 g per vial*

Must be constituted and further diluted.
See enclosed package insert for preparation instructions.

For Intravenous Infusion Only

*Each vial contains imipenem 500 mg (equivalent to 530 mg imipenem monohydrate), cilastatin 500 mg (equivalent
to 531 mg cilastatin sodium), and relebactam 250 mg (equivalent to 263 mg relebactam monohydrate).
Inactive ingredient: 20 mg sodium bicarbonate added to each vial as a buffer.

25 single-dose vials

Rx only